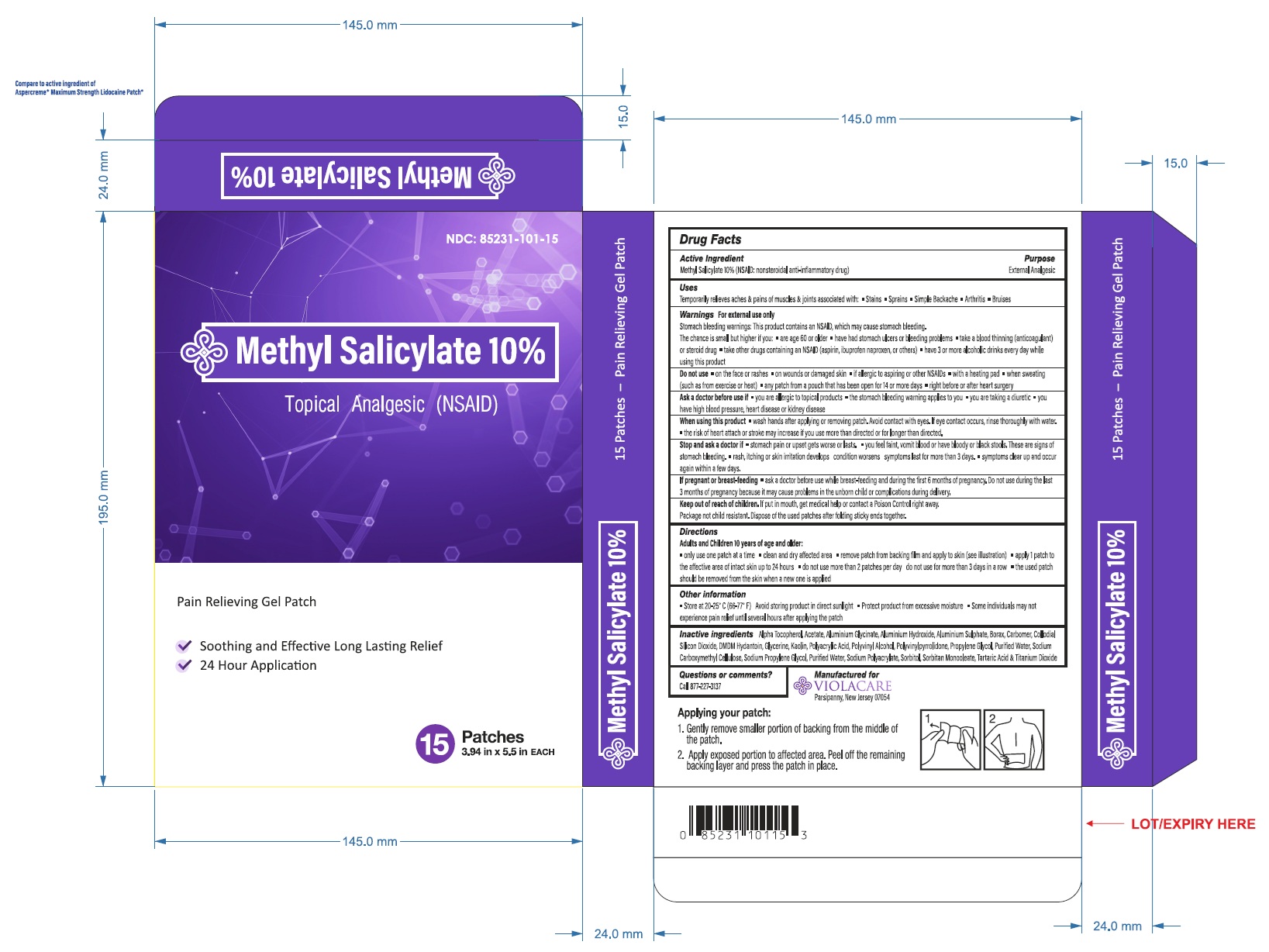 DRUG LABEL: Methyl Salicylate 10%
NDC: 85231-101 | Form: PATCH
Manufacturer: ViolaCare, Inc.
Category: otc | Type: HUMAN OTC DRUG LABEL
Date: 20250607

ACTIVE INGREDIENTS: METHYL SALICYLATE 10 g/100 g
INACTIVE INGREDIENTS: ALPHA-TOCOPHEROL ACETATE; ALUMINUM HYDROXIDE; CARBOMER 940; DMDM HYDANTOIN; GLYCERIN; KAOLIN; POLYACRYLIC ACID (250000 MW); POLYVINYL ALCOHOL (100000 MW); WATER; SODIUM POLYACRYLATE (8000 MW); SORBITOL; SORBITAN MONOOLEATE; TARTARIC ACID; TITANIUM DIOXIDE

Methyl Salicylate 10% Patch

Drug Facts

Active ingredients:

Methyl Salicylate 10% (NSAID: nonsteroidal anti-inflammatory drug)

Purpose

External analgesic

Uses

Temporarily relieves aches & pains of muscles & joints associated with:

- Stains
- Sprains
- Simple Backache
- Arthritis
- Bruises

Warnings

For external use only

Stomach bleeding warning: This product contains an NSAID, which may cause stomach bleeding.

The chance is small but higher if you:

- are age 60 or older
- have had stomach ulcers or bleeding problems
- take a blood thinning (anticoagulant) or steroid drug
- take other drugs containing as NSAID (aspirin, ibuprofen, naproxen, or others)
- have 3 or more alcoholic drinks every day while using this product

Do not use

- on the face or rashes
- on wounds or damaged skin
- if allergic to aspirin or other NSAIDs
- with a heating pad
- when sweating (such as from exercise or heat)
- any patch from a pouch that has been open for 14 or more days
- right before or after heat surgery

Ask a doctor before use if

- you are allergic to topical products
- the stomach bleeding warning applies to you
- you are taking a diuretic
- you have high blood pressure, heart disease or kidney disease

When using this product

- wash hands after applying or removing patch. Avoid contact with eyes. If eye contact occurs, rinse thoroughly with the water.
- the risk of heart attack or stroke may increase if you use more than directed or for longer than directed.

Stop and ask a doctor if

- stomach pain or upset gets worse or lasts
- you feel faint, vomit blood or have bloody or black stools, These are signs of stomach bleeding.
- rash, itching or skin irritation develops condition worsens symptoms last for more than 3 days
- symptoms clear up and occur again within a few days.

PREGNANCY OR BREAST FEEDING

If pregnant or breast-feeding,ask a doctor before use while breast-feeding and during the first 6 months of pregnancy. Do not use during the last 3 months of pregnancy because it may cause problems in the unborn child or complications during delivery.

Keep out of reach of children. If put in mouth, get medical help or contact a Poison Control right away. Package not child resistant. Dispose of the used patches after folding sticky ends together.

Directions

Adults and Children 10 years of age and older:

- only use one patch at a time
- clean and dry affected area
- remove patch from backing film and apply to skin (see illustration)
- apply 1 patch to the affective area of intact skin up to 24 hours.
- do not use more than 2 patches per day do not use for more than 3 days in a row
- the used patch should be removed from the skin when a new one is applied

Other information

- Store at 20-25°C (66-77°F)
- Avoid storing product in direct sunlight
- Protect product from excessive moisture
- Some individuals may not experience pain relief until several hours after applying the patch

Inactive ingredients

Alpha Tocopherol Acetate, Aluminum Glycinate, Aluminum Hydroxide, Aluminum Sulphate, Borax, Carbomer, Collodial Silicon Dioxide, DMDM Hydantoin, Glycerin, Kaolin, Polyacrylic Acid, Polyvinyl Alcohol, Polyvinylpyrrolidone, Propylene Glycol, Purified Water, Sodium Carboxymethyl Cellulose, Sodium Propylene Glycol, Sodium Polyacrylate, Sorbitol, Sorbitan Monooleate, Tartric Acid & Titanium Dioxide

Questions or comments?

Call 877-227-3137

PRINCIPAL DISPLAY PANEL

NDC 85231-101-15

METHYL SALICYLATE 10%
Topical Analgesic (NSAID)

Pain Relieving Gel Patch

Soothing and Effective Long Lasting Relief

24 Hour Application

15 Patches

3.94 in x 5.5 in EACH

Packaged For:

ViolaCare Inc.

Parsippany, New Jersey, 07054